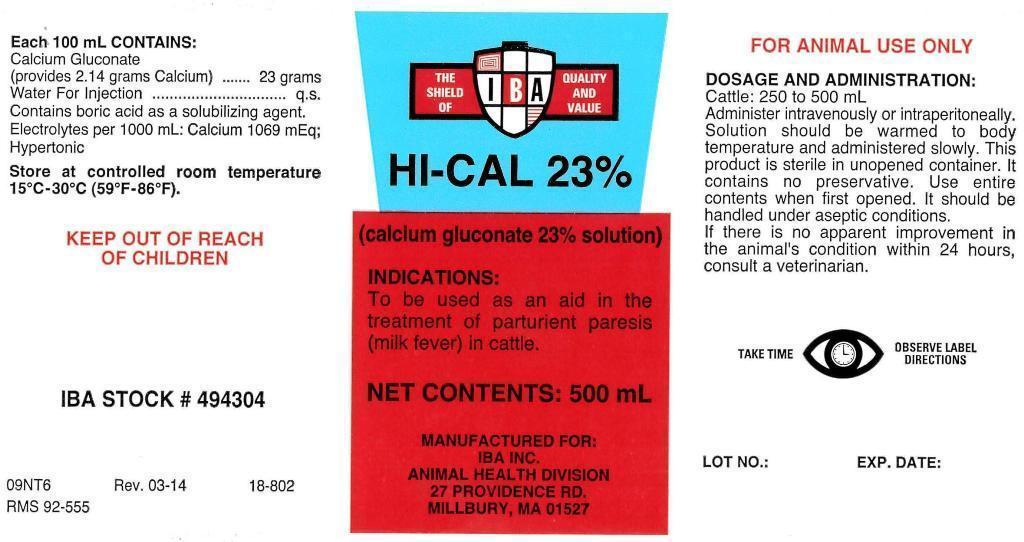 DRUG LABEL: Calcium Gluconate
NDC: 29983-2404 | Form: INJECTION, SOLUTION
Manufacturer: IBA Inc.
Category: animal | Type: OTC ANIMAL DRUG LABEL
Date: 20140602

ACTIVE INGREDIENTS: CALCIUM GLUCONATE 23 g/100 mL

HI-CAL 23%

Each 100 mL CONTAINS:

Calcium Gluconate
(provides 2.14 grams Calcium) ...... 23 grams
Water For Injection................................q.s.

INACTIVE INGREDIENT

Contains boric acid as a solubilizing agent.
Electrolytes per 1000 mL: Calcium 1069 mEq;
Hypertonic

STORAGE AND HANDLING

Store at controlled room temperature 15 degrees C - 30 degrees C (59 degrees F - 86 degrees F).

KEEP OUT OF REACH OF CHILDREN

INFORMATION FOR OWNERS/CAREGIVERS

IBA STOCK # 494304

09NT6 Rev. 03-14 18-802

RMS 92-555

(calcium gluconate 23% solution)

NET CONTENTS: 500 mL

MANUFACTURED FOR:
IBA INC.
ANIMAL HEALTH DIVISION
27 PROVIDENCE RD.
MILLBURY, MA 01527

LOT NO.: EXP. DATE:

INDICATIONS:

To be used as an aid in the treatment of parturient paresis (milk fever) in cattle.

GENERAL PRECAUTIONS

FOR ANIMAL USE ONLY

DOSAGE AND ADMINISTRATION:

Cattle: 250 to 500 mL

Administer intravenously or intraperitoneally. Solution should be warmed to body temperature and administered slowly. This product is sterile in unopened container. It contains no preservative. Use entire contents when first opened. it should be handled under aseptic conditions. If there is no apparent improvement in the animal's condition within 24 hours, consult a veterinarian.

GENERAL PRECAUTIONS

TAKE TIME OBSERVE LABEL DIRECTIONS